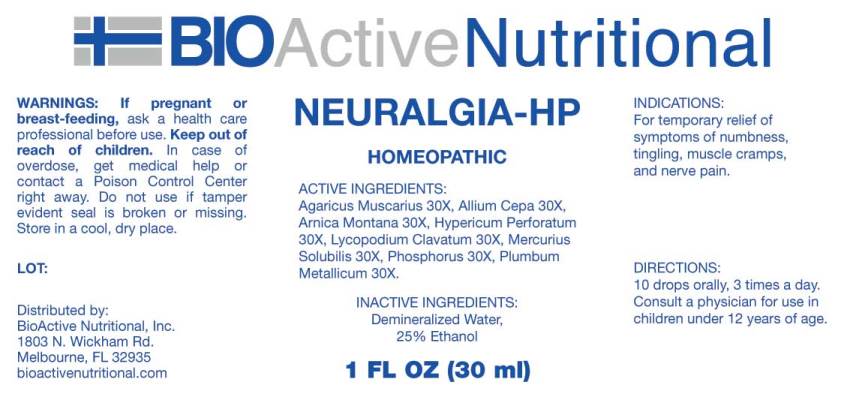 DRUG LABEL: Neuralgia
NDC: 43857-0381 | Form: LIQUID
Manufacturer: BioActive Nutritional, Inc.
Category: homeopathic | Type: HUMAN OTC DRUG LABEL
Date: 20170509

ACTIVE INGREDIENTS: AMANITA MUSCARIA FRUITING BODY 30 [hp_X]/1 mL; ONION 30 [hp_X]/1 mL; ARNICA MONTANA 30 [hp_X]/1 mL; HYPERICUM PERFORATUM 30 [hp_X]/1 mL; LYCOPODIUM CLAVATUM SPORE 30 [hp_X]/1 mL; MERCURIUS SOLUBILIS 30 [hp_X]/1 mL; PHOSPHORUS 30 [hp_X]/1 mL; LEAD 30 [hp_X]/1 mL
INACTIVE INGREDIENTS: WATER; ALCOHOL

Drug Facts:

ACTIVE INGREDIENTS:

Agaricus Muscarius 30X, Allium Cepa 30X, Arnica Montana 30X, Hypericum Perforatum 30X, Lycopodium Clavatum 30X, Mercurius Solubilis 30X, Phosphorus 30X, Plumbum Metallicum 30X.

INDICATIONS:

For temporary relief of symptoms of numbness, tingling, muscle cramps, and nerve pain.

WARNINGS:

If pregnant or breast-feeding, ask a health care professional before use.

Keep out of reach of children. In case of overdose, get medical help or contact a Poison Control Center right away.

Do not use if tamper evident seal is broken or missing.

Store in cool, dry place

Keep out of reach of children. In case of overdose, get medical help or contact a Poison Control Center right away.

DIRECTIONS:

10 drops orally, 3 times a day. Consult a physician for use in children under 12 years of age.

INDICATIONS:

For temporary relief of symptoms of numbness, tingling, muscle cramps, and nerve pain.

INACTIVE INGREDIENTS:

Demineralized Water, 25% Ethanol

QUESTIONS:

Distributed by:

BioActive Nutritional, Inc.

1803 N. Wickham Rd.

Melbourne, FL 32935

bioactivenutritional.com

PACKAGE LABEL DISPLAY:

BioActive Homeopathic

NEURALGIA-HP

HOMEOPATHIC

1 FL OZ (30 ml)